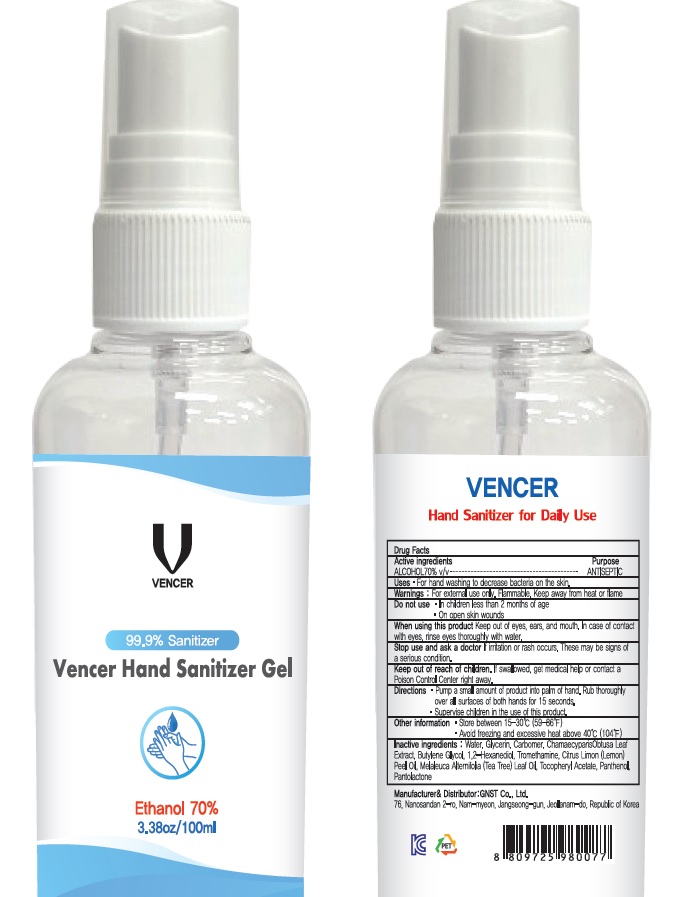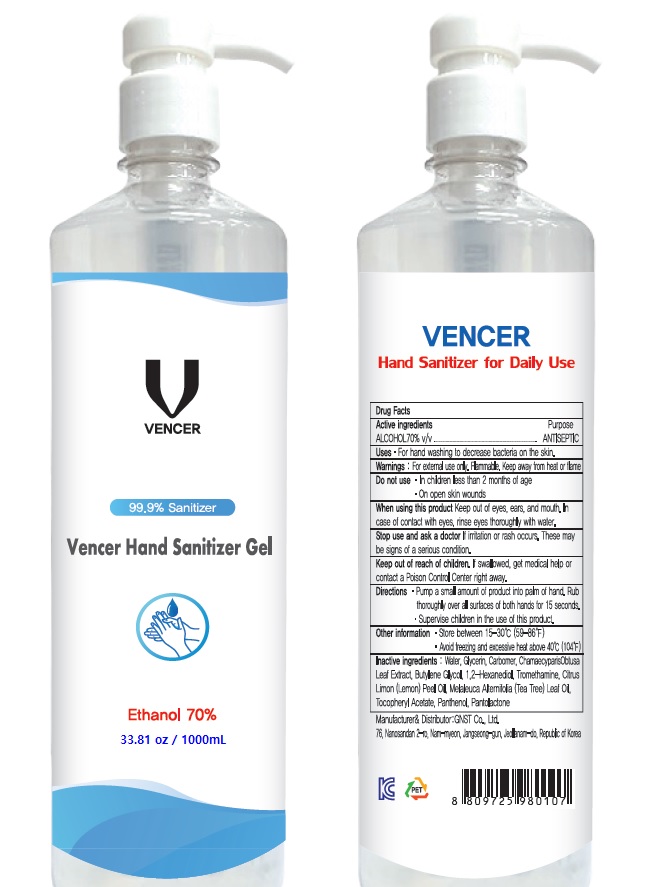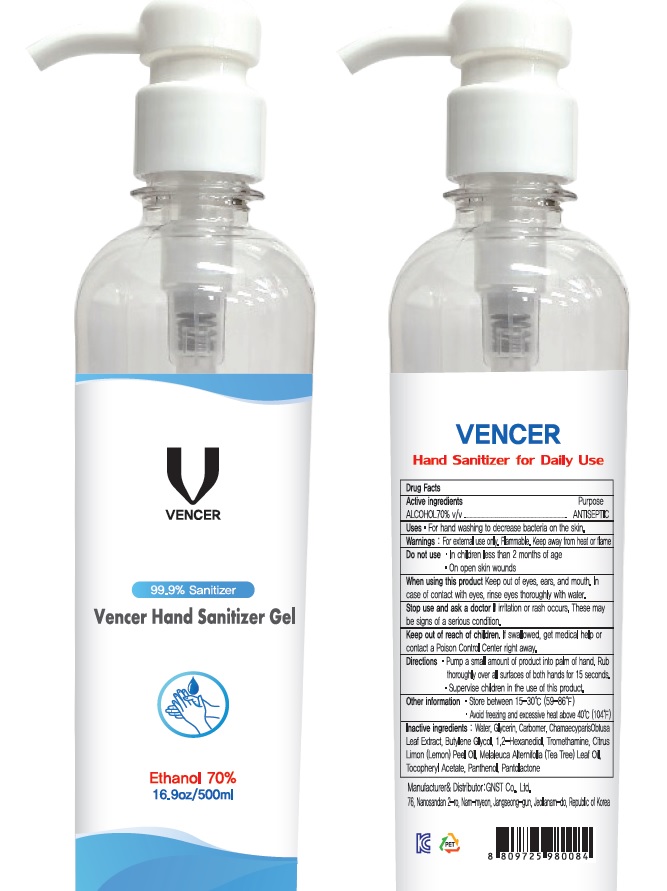 DRUG LABEL: VENCER Hand Sanitizer
NDC: 78454-010 | Form: GEL
Manufacturer: GNST Co.,Ltd.
Category: otc | Type: HUMAN OTC DRUG LABEL
Date: 20200602

ACTIVE INGREDIENTS: ALCOHOL 70 mL/100 mL
INACTIVE INGREDIENTS: Water; Glycerin; CARBOMER HOMOPOLYMER, UNSPECIFIED TYPE; CHAMAECYPARIS OBTUSA LEAF; Butylene Glycol; 1,2-Hexanediol; TROLAMINE; LEMON OIL; TEA TREE OIL; .ALPHA.-TOCOPHEROL ACETATE; Panthenol; PANTOLACTONE, (R)-

ACTIVE INGREDIENT

ALCOHOL 70% v/v

INACTIVE INGREDIENTS

Water, Glycerin, Carbomer, Chamaecyparis Obtusa Leaf Extract, Butylene Glycol, 1,2-Hexanediol, Tromethamine, Citrus Limon (Lemon) Peel Oil, Melaleuca Alternifolia (Tea Tree) Leaf Oil, Tocopheryl Acetate, Panthenol, Pantolactone

PURPOSE

ANTISEPTIC

WARNINGS

For external use only. Flammable. Keep away from heat or flame
--------------------------------------------------------------------------------------------------------
Do not use
• in children less than 2 months of age
• on open skin wounds
--------------------------------------------------------------------------------------------------------
When using this product keep out of eyes, ears, and mouth. In case of contact with eyes, rinse eyes thoroughly with water.
--------------------------------------------------------------------------------------------------------
Stop use and ask a doctor if irritation or rash occurs. These may be signs of a serious condition.

KEEP OUT OF REACH OF CHILDREN

If swallowed, get medical help or contact a Poison Control Center right away.

Uses

• For hand washing to decrease bacteria on the skin.

Directions

• Pump a small amount of product into palm of hand. Rub thoroughly over all surfaces of both hands for 15 seconds.
• Supervise children in the use of this product.

Other information

• Store between 15℃ to 30℃ (59℉ to 86℉)
• Avoid freezing and excessive heat above 40℃ (104℉)